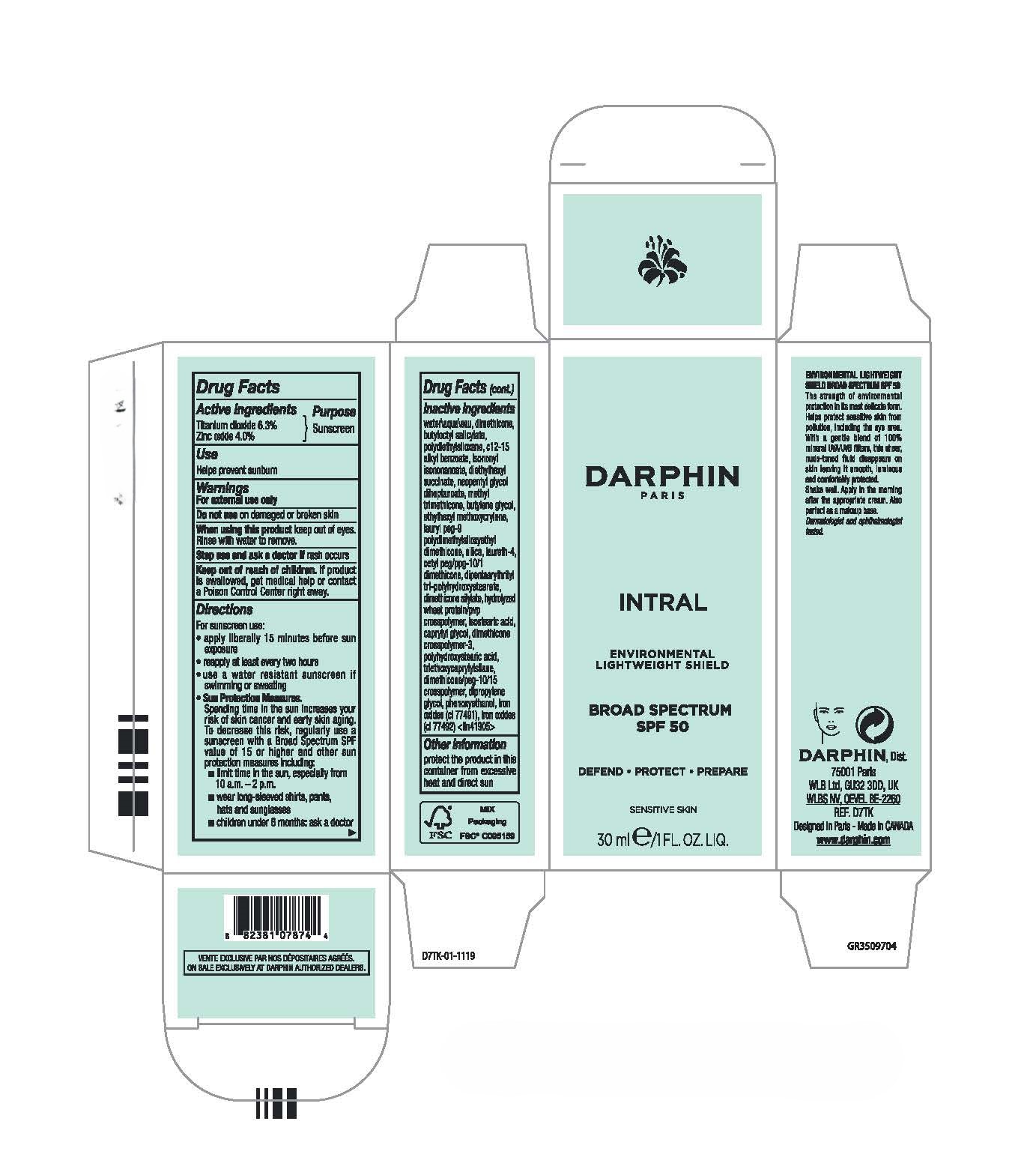 DRUG LABEL: INTRAL SENSITIVE SKIN ENVIRONMENTAL LIGHTWEIGHT SHIELD BROAD SPECTRUM SPF50
NDC: 16555-008 | Form: LOTION
Manufacturer: DARPHIN DIST.
Category: otc | Type: HUMAN OTC DRUG LABEL
Date: 20241111

ACTIVE INGREDIENTS: TITANIUM DIOXIDE 63 mg/1 mL; ZINC OXIDE 40 mg/1 mL
INACTIVE INGREDIENTS: FERRIC OXIDE RED; FERRIC OXIDE YELLOW; DIMETHICONE; BUTYLOCTYL SALICYLATE; PHENOXYETHANOL; ALKYL (C12-15) BENZOATE; ISONONYL ISONONANOATE; DIETHYLHEXYL SUCCINATE; NEOPENTYL GLYCOL DIHEPTANOATE; METHYL TRIMETHICONE; BUTYLENE GLYCOL; ETHYLHEXYL METHOXYCRYLENE; LAURYL PEG-9 POLYDIMETHYLSILOXYETHYL DIMETHICONE; SILICON DIOXIDE; LAURETH-4; DIPENTAERYTHRITYL TRI-POLYHYDROXYSTEARATE; ISOSTEARIC ACID; CAPRYLYL GLYCOL; TRIETHOXYCAPRYLYLSILANE; DIPROPYLENE GLYCOL; WATER

INTRAL SENSITIVE SKIN ENVIRONMENTAL LIGHTWEIGHT SHIELD BROAD SPECTRUM SPF50

Drug Facts

Active ingredients

Titanium dioxide 6.3%
Zinc oxide 4.0%

Purpose

Sunscreen

Uses

Helps prevent sunburn

Warnings

For external use only

Do not use on damaged or broken skin

When using this product keep out of eyes. Rinse with water to remove.

Stop use and ask a doctor if rash occurs

Keep out of reach of children. If product is swallowed, get medical help or contact a Poison Control Center right away.

Directions

For sunscreen use:

- apply liberally 15 minutes before sun exposure
- reapply at least every two hours
- use a water resistant sunscreen if swimming or sweating
- Sun Protection Measures.
  Spending time in the sun increases your risk of skin cancer and early skin aging. To decrease this risk, regularly use a sunscreen with a Broad Spectrum SPF value of 15 or higher and other sun protection measures including:
  - limit time in the sun, especially from 10 a.m. – 2 p.m.
  - wear long-sleeved shirts, pants, hats and sunglasses
  - children under 6 months: ask a doctor

Inactive ingredients

water\aqua\eau, dimethicone, butyloctyl salicylate, polydiethylsiloxane, c12-15 alkyl benzoate, isononyl isononanoate, diethylhexyl succinate, neopentyl glycol diheptanoate, methyl trimethicone, butylene glycol, ethylhexyl methoxycrylene, lauryl peg-9 polydimethylsiloxyethyl dimethicone, silica, laureth-4, cetyl peg/ppg-10/1 dimethicone, dipentaerythrityl tri-polyhydroxystearate, dimethicone silylate, hydrolyzed wheat protein/pvp crosspolymer, isostearic acid, caprylyl glycol, dimethicone crosspolymer-3, polyhydroxystearic acid, triethoxycaprylylsilane, dimethicone/peg-10/15 crosspolymer, dipropylene glycol, phenoxyethanol, iron oxides (ci 77491), iron oxides (ci 77492) <iln41905>

Other information

protect the product in this container from excessive heat and direct sun

PRINCIPAL DISPLAY PANEL - 30 ml Bottle Carton

DARPHIN
PARIS

INTRAL

ENVIRONMENTAL
LIGHTWEIGHT SHIELD

BROAD SPECTRUM
SPF 50

30 ml e/1 FL.OZ.LIQ.